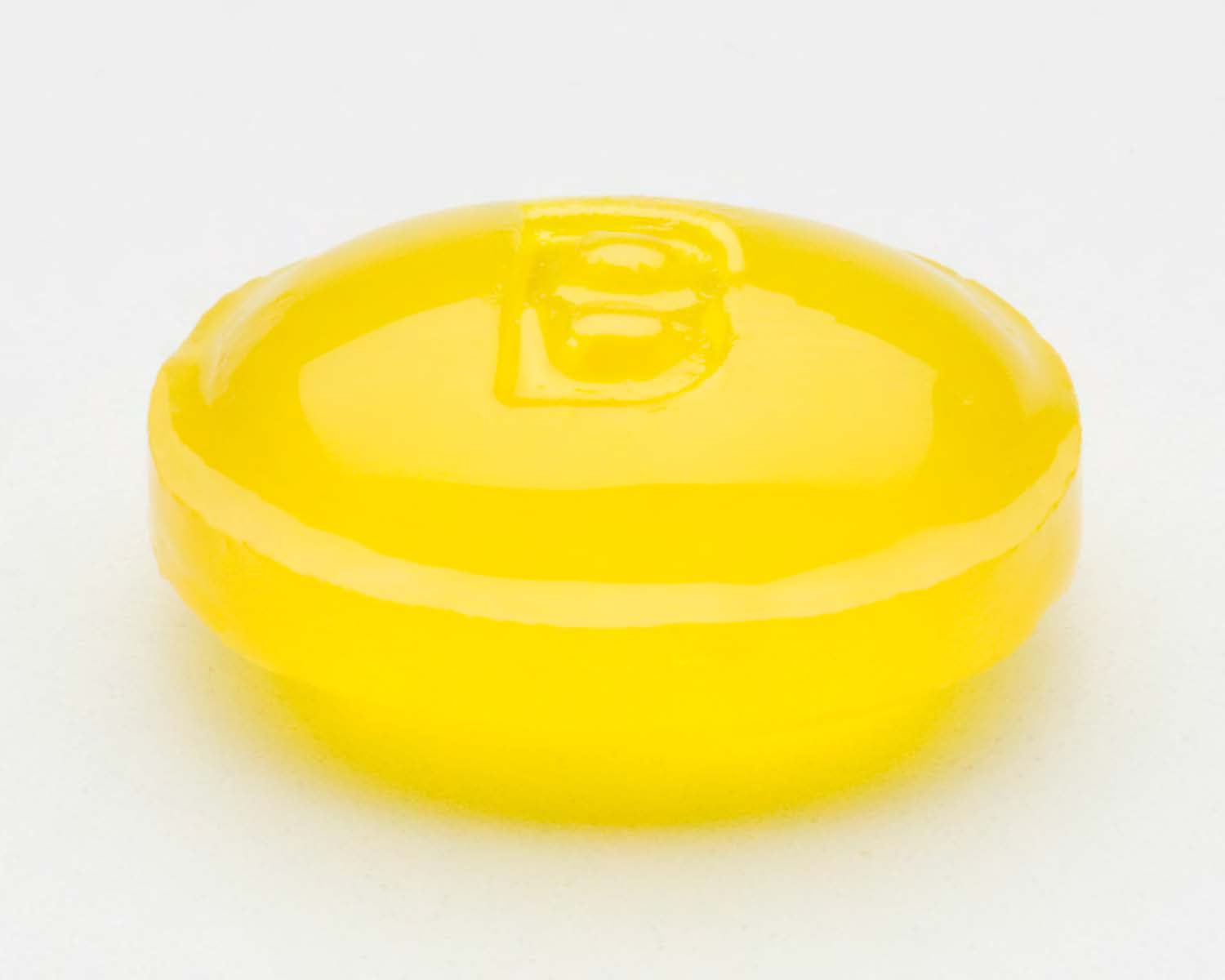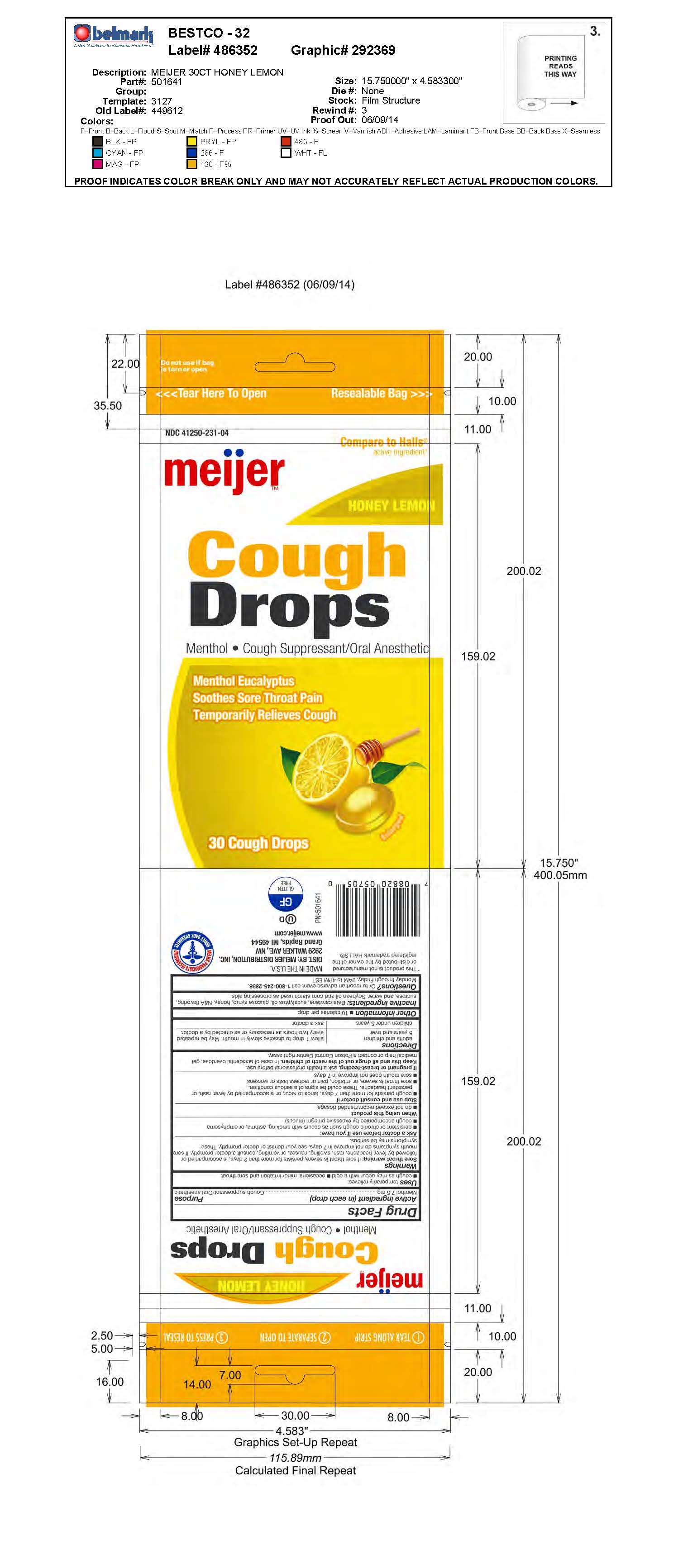 DRUG LABEL: Cherry Cough Drop
NDC: 41250-097 | Form: LOZENGE
Manufacturer: Meijer
Category: otc | Type: HUMAN OTC DRUG LABEL
Date: 20181101

ACTIVE INGREDIENTS: MENTHOL 7.5 mg/1 1
INACTIVE INGREDIENTS: WATER

Menthol 7.5mg

Active ingredient (in each drop)

Menthol 7.5mg

Purpose

Cough suppressant/

Oral anesthetic

INDICATIONS AND USAGE

Uses temporarily relieves:

- cough as may occur with a cold
- occasional minor irritation and sore throat

Warnings

Sore throat warning: if sore throat is severe, persists for

more than 2 days, is accompanied or followed by fever,

headache, rash, swelling, nausea, or vomiting, consult a

doctor promptly. If sore mouth symptoms do not improve

in 7 days, see your dentist or doctor promptly. These

symptoms may be serious.

Ask a doctor before use if you have:

- Persistent or chronic cough such as occurs with

smoking, asthma, or emphysema

- cough accompanied by excessive phlegm (mucus)

PREGNANCY OR BREAST FEEDING

If pregnant or breast-feeding, ask a health professional

before use.

Keep out of reach of children.

Directions

adults and children 5 years and over allow 1 drop to dissolve slowly in mouth. May be repeated every two hours as necessary or as directed by a doctor.

children under 5 years ask a doctor.

Other information 10 calories per drop

INACTIVE INGREDIENT

Inactive ingredients: Beta carotene, eucalyptus oil, glucose syrup, honey, N&A flavoring,

sucrose, and water. Soybean oil and corn starch used as processing aids.

QUESTIONS

Questions? or to report an adverse event call 1-800-245-2898.

Monday through Friday, 9AM to 4PM EST